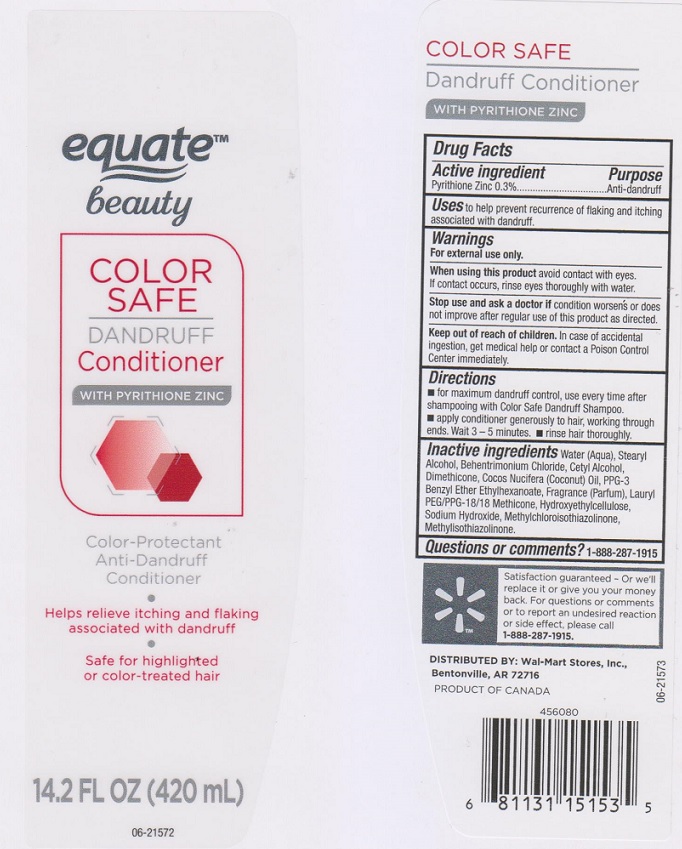 DRUG LABEL: Equate beauty Color Safe Dandruff Conditioner
NDC: 49035-440 | Form: LIQUID
Manufacturer: Wal-Mart Store Inc
Category: otc | Type: HUMAN OTC DRUG LABEL
Date: 20161219

ACTIVE INGREDIENTS: PYRITHIONE ZINC 3 mg/1 mL
INACTIVE INGREDIENTS: WATER; STEARYL ALCOHOL; BEHENTRIMONIUM CHLORIDE; CETYL ALCOHOL; DIMETHICONE; COCONUT OIL; PPG-3 BENZYL ETHER ETHYLHEXANOATE; LAURYL PEG/PPG-18/18 METHICONE; HYDROXYETHYL CELLULOSE (5000 CPS AT 1%); SODIUM HYDROXIDE; METHYLCHLOROISOTHIAZOLINONE; METHYLISOTHIAZOLINONE

Drug Facts

Active ingredient

Pyrithione Zinc 0.3%

Purpose

Anti-dandruff

Uses

to help prevent recurrence of flaking and itching associated with dandruff.

Warnings

For external use only.

When using this product

avoid contact with eyes. If contact occurs, rinse eyes thoroughly with water.

Stop use and ask a doctor if

condition worsens or does not improve after regular use of this product as directed.

Keep out of reach of children.

In case of accidental ingestion, get medical help or contact a Poison Control Center immediately.

Directions

- for maximum dandruff control, use every time after shampooing with Color Safe Dandruff Shampoo.
- apply conditioner generously to hair, working through ends. Wait 3-5 minutes.
- rinse hair thoroughly.

Inactive ingredients

Water (Aqua), Stearyl Alcohol, Behentrimonium Chloride, Cetyl Alcohol, Dimethicone, Cocos Nucifera (Coconut) Oil, PPG-3 Benzyl Ether Ethylhexanoate, Fragrance (Parfum), Lauryl PEG/PPG-18/18 Methicone, Hydroxyethylcellulose, Sodium Hydroxide, Methylchloroisothiazolinone, Methylisothiazolinone.

Questions or comments?

1-888-287-1915